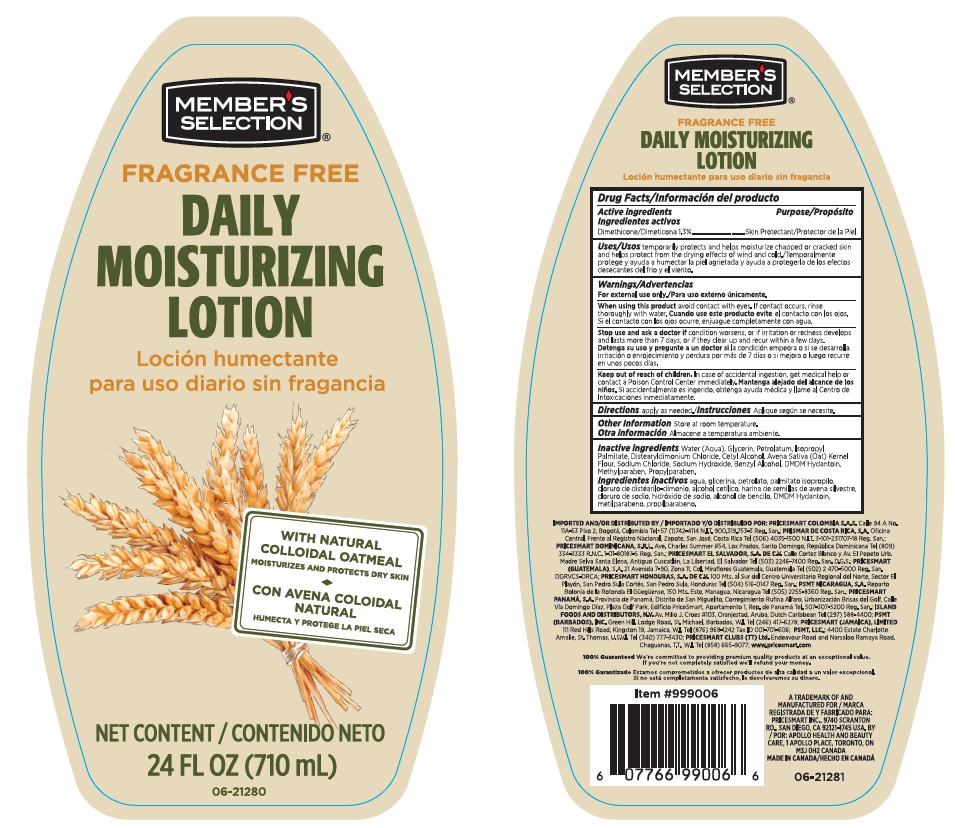 DRUG LABEL: Members Select Daily Moisturizing
NDC: 63148-561 | Form: LOTION
Manufacturer: Apollo Health and Beauty Care Inc.
Category: otc | Type: HUMAN OTC DRUG LABEL
Date: 20180329

ACTIVE INGREDIENTS: DIMETHICONE 13 mg/1 mL
INACTIVE INGREDIENTS: WATER; GLYCERIN; PETROLATUM; ISOPROPYL PALMITATE; DISTEARYLDIMONIUM CHLORIDE; CETYL ALCOHOL; OAT; SODIUM CHLORIDE; SODIUM HYDROXIDE; BENZYL ALCOHOL; DMDM HYDANTOIN; METHYLPARABEN; PROPYLPARABEN

Drug Facts

Active ingredient

Dimethicone 1.3%

Purpose

Skin protectant

Uses

temporarily protects and helps moisturize chapped or cracked skin and helps proect from the drying effects of wind and cold.

Warnings

For external use only

When using this product

avoid contact with eyes. If contact occurs, rinse thoroughly with water.

Stop use and ask a doctor if

condition worsens, or if irritation or redness develops and lasts more than 7 dyas, or if they clear up and recur within a few days.

Keep out of reach of children.

In case of accidental ingestion, get medical help or contact a Poison Control Center immediately.

Directions

apply as needed

Other information

store at room temperature.

Inactive ingredients

Water (Aqua), Glycerin, Petrolatum, Isopropyl Palmitate, Distearyldimonium Chloride, Cetyl Alcohol, Avena Sativa (Oat) Kernel Flour, Sodium Chloride, Sodium Hydroxide, Benzyl Alcohol DMDM Hydantoin, Metylparaben, Propylparaben.